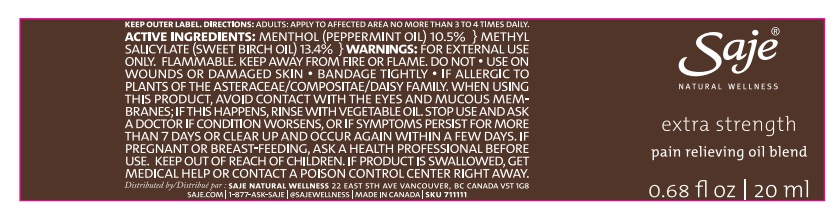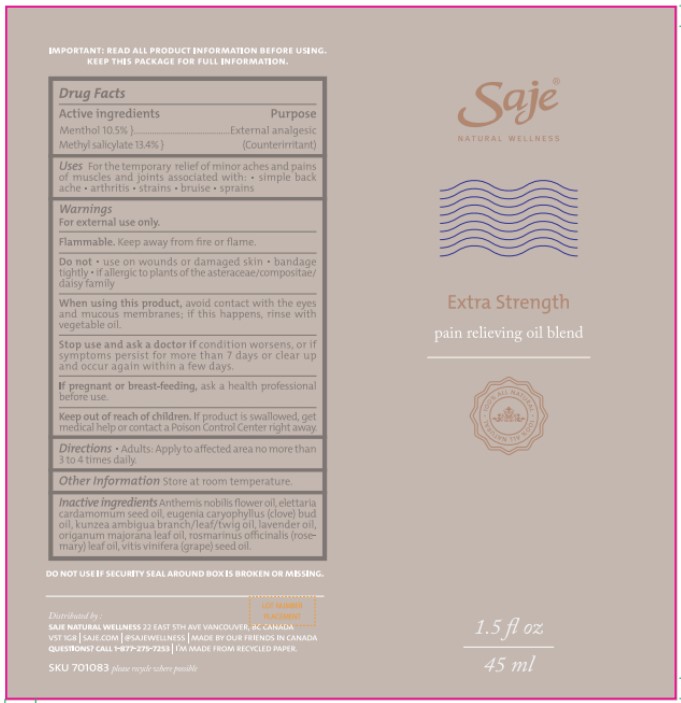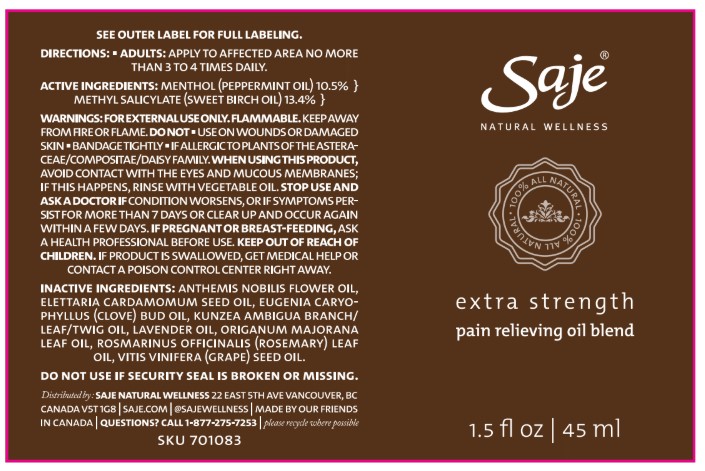 DRUG LABEL: Extra Strength
NDC: 70983-023 | Form: OIL
Manufacturer: Saje Natural Business Inc.
Category: otc | Type: HUMAN OTC DRUG LABEL
Date: 20251024

ACTIVE INGREDIENTS: MENTHOL 94.41 mg/1 mL; METHYL SALICYLATE 123.74 mg/1 mL
INACTIVE INGREDIENTS: CHAMAEMELUM NOBILE; KUNZEA AMBIGUA WHOLE; LAVENDER OIL; ORIGANUM MAJORANA; ROSEMARY OIL; TRIFOLIUM PRATENSE FLOWER; GRAPE SEED OIL; PEPPERMINT OIL; BETULA LENTA BARK; ELETTARIA CARDAMOMUM WHOLE

Extra Strength

ACTIVE INGREDIENT

Menthol 10.5%, Methyl Salicylate 13.4%

PURPOSE

External analgesic (Counterirritant)

INDICATIONS AND USAGE

For the temporary relief of minor aches and pains of muscles and joints associated with: • simple back ache • arthritis • strains • bruise • sprains

WARNINGS

For external use only

Flammable

Keep away from fire and flame

Do not use on wounds or damaged skin

Do not bandage tightly

Do not use if you are allergic to plants of the asteraceae/compositae/daisy family

WHEN USING

Avoid contact with eyes and mucous membranes; if this happens, rinse with vegetable oil

Stop use and ask a doctor if condition worsens, or if symptoms persist for more than 7 days or clear up and occur again within a few days.

PREGNANCY OR BREAST FEEDING

If pregnant or breastfeeding, ask a health professional before use.

Keep out of reach of children. If product swallowed, get medical help or contact a Poison Control Centre right way.

DOSAGE AND ADMINISTRATION

Adults: apply to affected area no more than 3 to 4 times daily.

STORAGE AND HANDLING

Store at room temperature.

INACTIVE INGREDIENT

Anthemis nobilis flower oil, elettaria cardamomum seed oil, kunzea ambigua branch/leaf/twig oil, lavender oil, origanum majorana leaf oil, rosmarinus officinalis (rosemary) leaf oil, syzygium aromaticum bud oil, vitis vinifera (grape) seed oil

OTHER SAFETY INFORMATION

Important: Read all product information before using. Keep this package for full information.
Do not use if security seal around bottle is broken or missing.
Questions? Call 1-877-275-7253
distributed by: saje natural wellness 22 east 5th ave vancouver, bc canada v5t 1g8 saje.com 1-877-ask-saje @sajewellness

DESCRIPTION

Extra Strength
Pain Relieving Oil Blend
0.68 fl oz (20 ml)

Extra Strength
Pain Relieving Oil Blend
1.5 fl oz (45 ml)